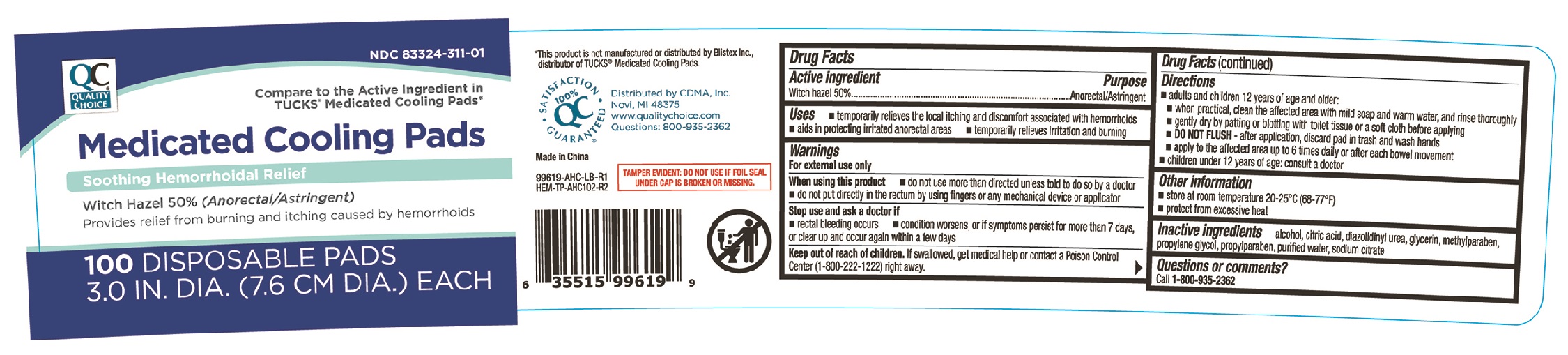 DRUG LABEL: QC Medicated Cooling
NDC: 83324-311 | Form: CLOTH
Manufacturer: Chain Drug Marketing Association, Inc.
Category: otc | Type: HUMAN OTC DRUG LABEL
Date: 20251219

ACTIVE INGREDIENTS: WITCH HAZEL 500 mg/1 1
INACTIVE INGREDIENTS: ALCOHOL; PROPYLENE GLYCOL; CITRIC ACID; GLYCERIN; DIAZOLIDINYL UREA; METHYLPARABEN; PROPYLPARABEN; WATER; SODIUM CITRATE

QC Medicated Cooling Pads 99619 for Hemorrhoidal Use 100ct

Active Ingredients Purpose

Witch Hazel 50%..........................................................Anorectal/Astringent

Uses

- temporarily relieves the local itching and discomfort associated with hemorrhoids
- aids in protecting irritated anorectal areas
- temporarily relieves irritation and burning

Warnings

For external use only

When using this product

- do not use more than directed unless told to do so by a doctor
- do not put directly in the rectum by using fingers or any mechanical device or applicator

Stop use and ask a doctor if

- rectal bleeding occurs
- condition worsens, or if symptoms persist for more than 7 days, or clear up and occur again within a few days

Keep out of reach of children. If swallowed, get medical help or contact a Poison Control Center (1-800-222-1222) right away.

Directions

- adults and children 12 years of age and older:
- when practical, clean the affected area with mild soap and warm water, and rinse thoroughly
- gently dry by patting or blotting with toilet tissue or soft cloth before applying
- DO NOT FLUSH - after application, discard pad in trash and wash hands
- apply to the affected area up to 6 times daily or after each bowel movement
- children under 12 years of age: consult a doctor

Other information

- store at room temperature 20-25°C (68-77°F)
- protect from excessive heat

Inactive ingredient

alcohol, citric acid, dizaolidinyl urea, glycerin, methylparaben, propylene glycol, propylparaben, purified water, sodium citrate

DOSAGE AND ADMINISTRATION

Distributed by: CDMA, Inc.

Novi, MI 48375

Made in China